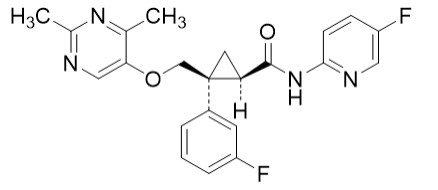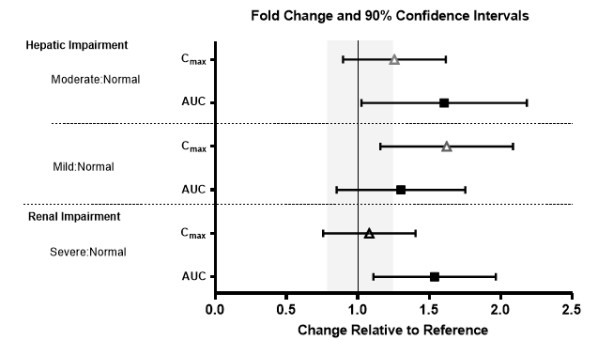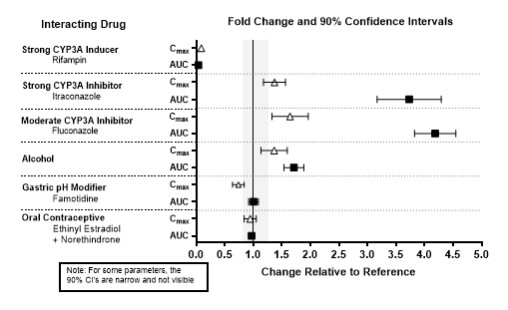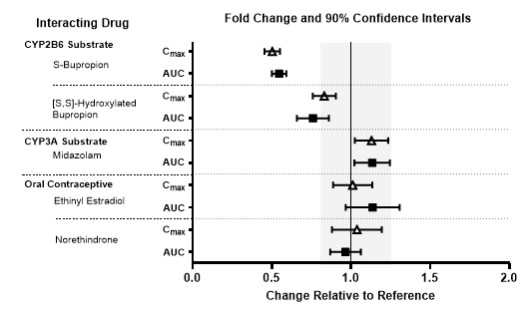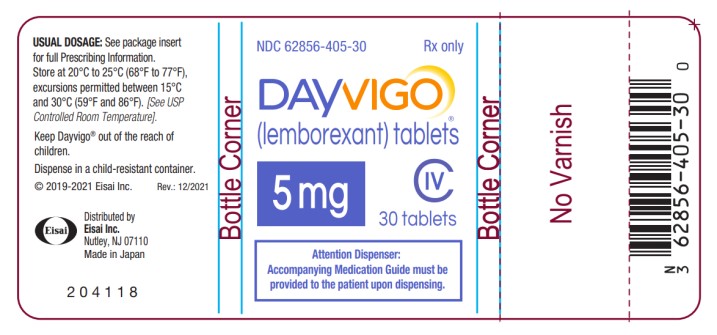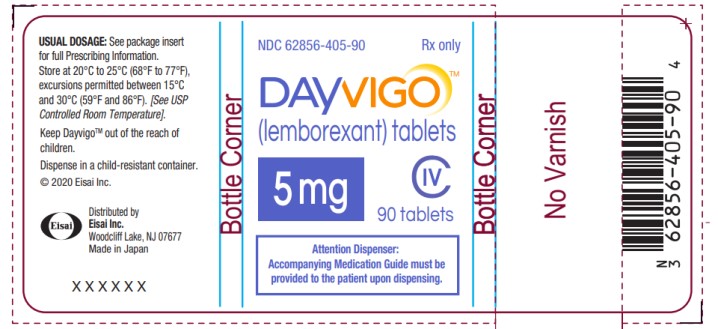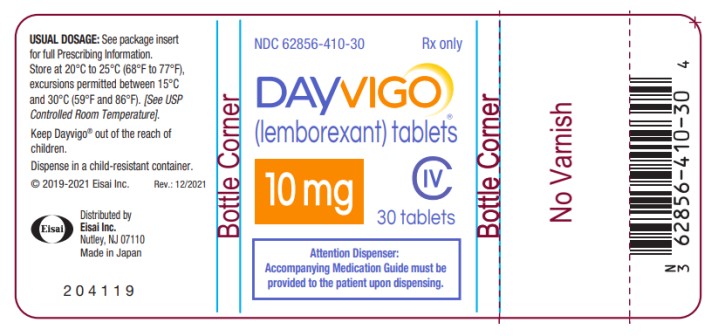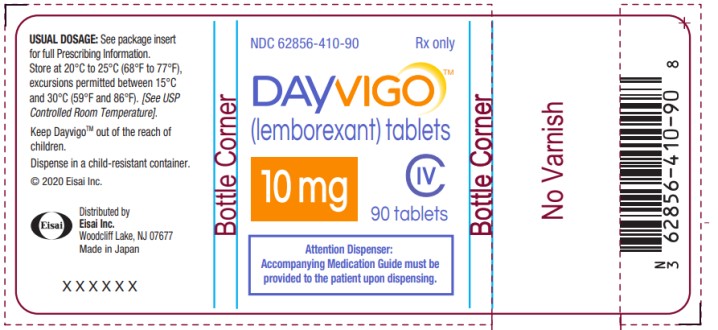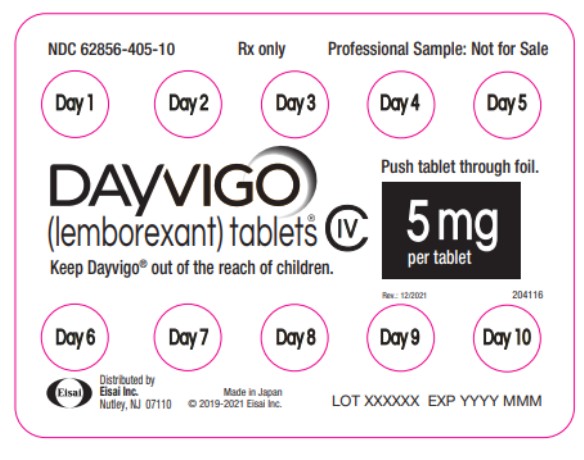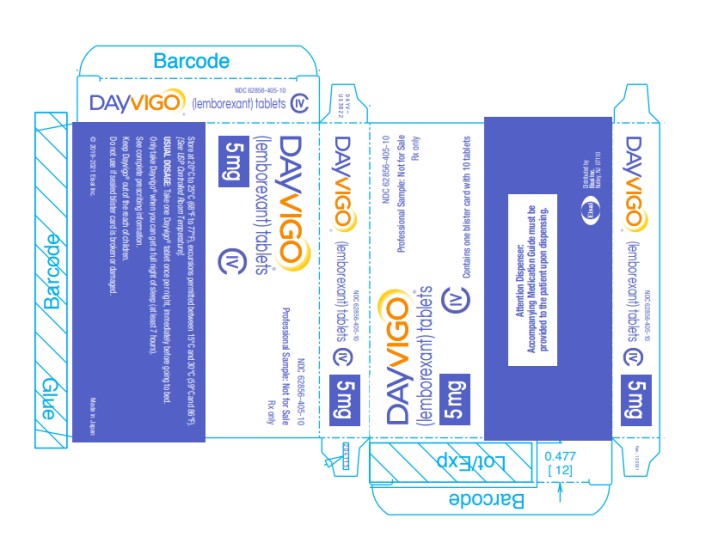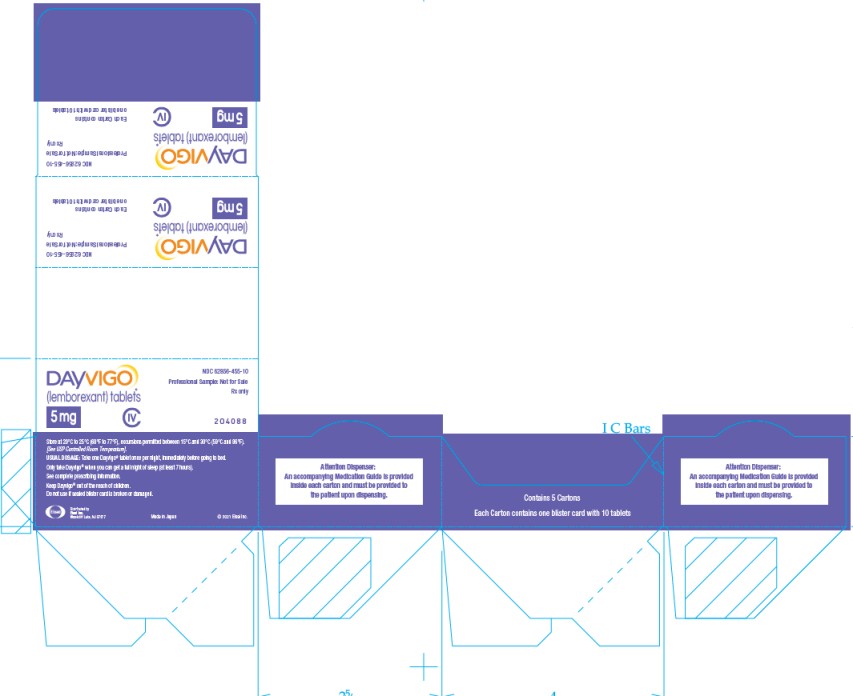 DRUG LABEL: DAYVIGO
NDC: 62856-405 | Form: TABLET, FILM COATED
Manufacturer: Eisai Inc.
Category: prescription | Type: HUMAN PRESCRIPTION DRUG LABEL
Date: 20250224
DEA Schedule: CIV

ACTIVE INGREDIENTS: LEMBOREXANT 5 mg/1 1
INACTIVE INGREDIENTS: HYDROXYPROPYL CELLULOSE (45000 WAMW); LACTOSE MONOHYDRATE; LOW-SUBSTITUTED HYDROXYPROPYL CELLULOSE (11% HYDROXYPROPYL; 120000 MW); MAGNESIUM STEARATE; HYPROMELLOSE 2910 (6 MPA.S); POLYETHYLENE GLYCOL 8000; TALC; TITANIUM DIOXIDE; WATER; FERRIC OXIDE YELLOW

HIGHLIGHTS OF PRESCRIBING INFORMATION

These highlights do not include all the information needed to use DAYVIGO® safely and effectively. See full prescribing information for DAYVIGO®.
DAYVIGO® (lemborexant) tablets, for oral use, CIV
Initial U.S. Approval: 2019

1 INDICATIONS AND USAGE

DAYVIGO is an orexin receptor antagonist indicated for the treatment of adult patients with insomnia, characterized by difficulties with sleep onset and/or sleep maintenance. (1)

2 DOSAGE AND ADMINISTRATION

- Recommended dose is 5 mg taken no more than once per night, immediately before going to bed, with at least 7 hours remaining before the planned time of awakening. Dosage may be increased to 10 mg based on clinical response and tolerability. (2.1)
- The maximum recommended dose is 10 mg once daily. (2.1)
- Time to sleep onset may be delayed if taken with or soon after a meal. (2.1)
- Hepatic Impairment: (2.3)
  ○ Moderate hepatic impairment: Initial and maximum recommended dosage is 5 mg no more than once per night.
  ○ Severe hepatic impairment: Not recommended.

3 DOSAGE FORMS AND STRENGTHS

Tablets: 5 mg, 10 mg (3)

4 CONTRAINDICATIONS

DAYVIGO is contraindicated in patients with narcolepsy. (4)

5 WARNINGS AND PRECAUTIONS

- CNS Depressant Effects and Daytime Impairment: Impairs alertness and motor coordination including morning impairment. Risk increases with dose and use with other central nervous system (CNS) depressants. For patients taking DAYVIGO 10 mg, caution against next-day driving and other activities requiring complete mental alertness. (5.1)
- Sleep Paralysis, Hypnagogic/Hypnopompic Hallucinations, and Cataplexy-like Symptoms: May occur with use of DAYVIGO. (5.2)
- Complex Sleep Behaviors: Behaviors including sleep-walking, sleep-driving, and engaging in other activities while not fully awake may occur. Discontinue immediately if a complex sleep behavior occurs. (5.3)
- Compromised Respiratory Function: Effect on respiratory function should be considered. (5.4, 8.8)
- Worsening of Depression/Suicidal Ideation: Worsening of depression or suicidal thinking may occur. Prescribe the lowest number of tablets feasible to avoid intentional overdosage. (5.5)
- Need to Evaluate for Co-morbid Diagnoses: Reevaluate if insomnia persists after 7 to 10 days of treatment. (5.6)

6 ADVERSE REACTIONS

The most common adverse reaction (reported in ≥5% of patients treated with DAYVIGO and at least twice the rate of placebo) was somnolence. (6.1)

To report SUSPECTED ADVERSE REACTIONS, contact Eisai Inc. at 1-888-274-2378 or FDA at 1-800-FDA-1088 or www.fda.gov/medwatch.

7 DRUG INTERACTIONS

- Strong or moderate CYP3A inhibitors: Avoid concomitant use. (7.1)
- Weak CYP3A inhibitors: The maximum recommended dose is 5 mg. (2.2, 7.1)
- Strong or moderate CYP3A inducers: Avoid concomitant use. (7.1)

FULL PRESCRIBING INFORMATION

1 INDICATIONS AND USAGE

DAYVIGO is indicated for the treatment of adult patients with insomnia, characterized by difficulties with sleep onset and/or sleep maintenance [see Clinical Studies (14.1)].

2 DOSAGE AND ADMINISTRATION

2.1 Dosing Information

The recommended dosage of DAYVIGO is 5 mg taken no more than once per night, immediately before going to bed, with at least 7 hours remaining before the planned time of awakening. The dose may be increased to the maximum recommended dose of 10 mg based on clinical response and tolerability. Time to sleep onset may be delayed if taken with or soon after a meal [see Clinical Pharmacology (12.3)].

2.2 Dosage Recommendations for Concomitant Use with CYP3A Inhibitors or CYP3A Inducers

Co-administration with Strong or Moderate CYP3A Inhibitors

Avoid concomitant use of DAYVIGO with strong or moderate CYP3A inhibitors [see Drug Interactions (7.1), Clinical Pharmacology (12.3)].

Co-administration with Weak CYP3A Inhibitors

The maximum recommended dosage of DAYVIGO is 5 mg no more than once per night when co-administered with weak CYP3A inhibitors [see Drug Interactions (7.1), Clinical Pharmacology (12.3)].

Co-administration with Strong or Moderate CYP3A Inducers

Avoid concomitant use of DAYVIGO with strong or moderate CYP3A inducers [see Drug Interactions (7.1), Clinical Pharmacology (12.3)].

2.3 Dosage Recommendations for Patients with Hepatic Impairment

The maximum recommended dose of DAYVIGO is 5 mg no more than once per night in patients with moderate hepatic impairment [see Use in Specific Populations (8.7), Clinical Pharmacology (12.3)].

DAYVIGO is not recommended in patients with severe hepatic impairment [see Use in Specific Populations (8.7)].

3 DOSAGE FORMS AND STRENGTHS

DAYVIGO (lemborexant) tablets are available as:

- 5 mg tablets: pale yellow, round, biconvex, film-coated tablets, and debossed with "5" on one side and "LЄM" on the other side.
- 10 mg tablets: orange, round, biconvex, film-coated tablets, and debossed with "10" on one side and "LЄM" on the other side.

4 CONTRAINDICATIONS

DAYVIGO is contraindicated in patients with narcolepsy.

5 WARNINGS AND PRECAUTIONS

5.1 CNS Depressant Effects and Daytime Impairment

DAYVIGO is a central nervous system (CNS) depressant that can impair daytime wakefulness even when used as prescribed. CNS depressant effects may persist in some patients for up to several days after discontinuing DAYVIGO. Prescribers should advise patients about the potential for next-day somnolence.

Driving ability was impaired in some subjects taking DAYVIGO 10 mg [see Clinical Studies (14.2)]. The risk of daytime impairment is increased if DAYVIGO is taken with less than a full night of sleep remaining or if a higher than recommended dose is taken [see Dosage and Administration (2.1)]. If DAYVIGO is taken in these circumstances, patients should be cautioned against driving and other activities requiring complete mental alertness.

Co-administration with other CNS depressants (e.g., benzodiazepines, opioids, tricyclic antidepressants, alcohol) increases the risk of CNS depression, which can cause daytime impairment. Dosage adjustments of DAYVIGO and of concomitant CNS depressants may be necessary when administered together because of potentially additive effects. The use of DAYVIGO with other drugs to treat insomnia is not recommended. Patients should be advised not to consume alcohol in combination with DAYVIGO because of additive effects [see Drug Interactions (7.1)].

Because DAYVIGO can cause drowsiness, patients, particularly the elderly, are at a higher risk of falls.

5.2 Sleep Paralysis, Hypnagogic/Hypnopompic Hallucinations, and Cataplexy-like Symptoms

Sleep paralysis, an inability to move or speak for up to several minutes during sleep-wake transitions, and hypnagogic/hypnopompic hallucinations, including vivid and disturbing perceptions, can occur with the use of DAYVIGO. Prescribers should explain the nature of these events to patients when prescribing DAYVIGO.

Symptoms similar to mild cataplexy can occur with DAYVIGO. Such symptoms can include periods of leg weakness lasting from seconds to a few minutes, can occur either at night or during the day, and may not be associated with an identified triggering event (e.g., laughter or surprise).

5.3 Complex Sleep Behaviors

Complex sleep behaviors, including sleep-walking, sleep-driving, and engaging in other activities while not fully awake (e.g., preparing and eating food, making phone calls, having sex), have been reported to occur with the use of hypnotics such as DAYVIGO. These events can occur in hypnotic-naïve as well as in hypnotic-experienced persons. Patients usually do not remember these events. Complex sleep behaviors may occur following the first or any subsequent use of DAYVIGO, with or without the concomitant use of alcohol and other CNS depressants [see Drug Interactions (7.1)]. Discontinue DAYVIGO immediately if a patient experiences a complex sleep behavior.

5.4 Patients with Compromised Respiratory Function

DAYVIGO has been studied in mild to severe Obstructive Sleep Apnea (OSA) and moderate to severe Chronic Obstructive Pulmonary Disease (COPD) in short-term clinical trials. The effect of DAYVIGO on respiratory function should be considered if prescribed to patients with compromised respiratory function [see Use in Specific Populations (8.8)].

5.5 Worsening of Depression/Suicidal Ideation

In clinical studies of DAYVIGO in patients with insomnia, the incidence of suicidal ideation or any suicidal behavior, as assessed by questionnaire, was higher in patients receiving DAYVIGO than in those receiving placebo (0.3% for DAYVIGO 10 mg, 0.4% for DAYVIGO 5 mg, and 0.2% for placebo).

In primarily depressed patients treated with hypnotics, worsening of depression and suicidal thoughts and actions (including completed suicides) have been reported. Suicidal tendencies may be present in such patients and protective measures may be required. Intentional overdose is more common in this group of patients; therefore, the lowest number of tablets that is feasible should be prescribed at any one time.

The emergence of any new behavioral sign or symptom of concern requires careful and immediate evaluation.

5.6 Need to Evaluate for Co-morbid Diagnoses

Because sleep disturbances may be the presenting manifestation of a medical and/or psychiatric disorder, treatment of insomnia should be initiated only after careful evaluation of the patient. The failure of insomnia to remit after 7 to 10 days of treatment may indicate the presence of a primary psychiatric and/or medical illness that should be evaluated. Worsening of insomnia or the emergence of new cognitive or behavioral abnormalities may be the result of an unrecognized underlying psychiatric or medical disorder and can emerge during the course of treatment with sleep-promoting drugs such as DAYVIGO.

6 ADVERSE REACTIONS

The following clinically significant adverse reactions are discussed in detail in other sections of the labeling:

- CNS Depressant Effects and Daytime Impairment [see Warnings and Precautions (5.1)]
- Sleep Paralysis, Hypnagogic/Hypnopompic Hallucinations, and Cataplexy-like Symptoms [see Warnings and Precautions (5.2)]
- Complex Sleep Behaviors [see Warnings and Precautions (5.3)]
- Patients with Compromised Respiratory Function [see Warnings and Precautions (5.4)]
- Worsening of Depression/Suicidal Ideation [see Warnings and Precautions (5.5)]

6.1 Clinical Trials Experience

Because clinical trials are conducted under widely varying conditions, adverse reaction rates observed in the clinical trials of a drug cannot be directly compared to rates in the clinical trials of another drug and may not reflect the rates observed in practice.

The safety of DAYVIGO was evaluated in 1418 adult patients with insomnia disorder (age 18 to 88 years) from two controlled efficacy trials (Study 1 and Study 2). Study 1 was a 6-month placebo-controlled trial assessing DAYVIGO 5 or 10 mg once nightly, followed by a 6-month parallel-group extension period in which patients initially treated with DAYVIGO continued on the same dose, and patients who received placebo were re-randomized to receive DAYVIGO 5 or 10 mg once nightly. In Study 1, 434 patients were treated with DAYVIGO for one year. Study 2 was a 30-day placebo- and active-controlled trial assessing DAYVIGO 5 or 10 mg once nightly.

Adverse Reactions Resulting in Discontinuation of Treatment

The frequencies of discontinuation due to adverse reactions in Study 1 (the first 30 days) and Study 2 were 2.6% and 1.4% for patients treated with 10 mg and 5 mg DAYVIGO, respectively, compared to 1.5% for patients in the placebo group. The most common adverse reactions leading to discontinuation of DAYVIGO were somnolence (1.0% for 10 mg, 0.7% for 5 mg, and 0.4% for placebo) and nightmares (0.3% for 10 mg, 0.3% for 5 mg, and 0% for placebo).

The frequencies of discontinuation due to adverse reactions in the 6-month placebo-controlled period of Study 1 were 8.3% and 4.1% for patients treated with DAYVIGO 10 mg and 5 mg, respectively, compared to 3.8% for patients in the placebo group. The most common reasons for discontinuation of DAYVIGO and occurring in more than one patient within a treatment arm were somnolence (2.9% for 10 mg, 1.0% for 5 mg, and 0.6% for placebo), nightmares (1.3% for 10 mg, 0.3% for 5 mg, and 0% for placebo), and palpitations (0.6% for 10 mg, 0% for 5 mg, and 0% for placebo).

Most Common Adverse Reactions

The most common adverse reaction (reported in 5% or more of patients treated with DAYVIGO and at least twice the rate of placebo) in Study 1 (the first 30 days) and Study 2 was somnolence (10% for DAYVIGO 10 mg, 7% for DAYVIGO 5 mg, and 1% for placebo).

Table 1 presents the adverse reactions based on the pooled data from the first 30 days of Study 1 (6-month controlled efficacy trial) and Study 2 (1-month controlled efficacy trial) where the incidence was ≥2% in DAYVIGO-treated patients and greater than in placebo-treated patients.

Table 1: Adverse Reactions Reported in ≥2% of DAYVIGO-Treated Patients and at a Greater Frequency than Placebo-Treated Patients During the First 30 Days of Study 1 and Study 2
 |  | DAYVIGO
 | Placebo | 5 mg | 10 mg
 | n=528 | n=580 | n=582
 | (%) | (%) | (%)
Somnolence or fatigue* | 1.3 | 6.9 | 9.6
Headache | 3.4 | 5.9 | 4.5
Nightmare or abnormal dreams | 0.9 | 0.9 | 2.2

*Combines preferred terms somnolence, lethargy, fatigue, sluggishness

Other Adverse Reactions Observed During Clinical Trials (Studies 1 and 2)

Other adverse reactions of <2% incidence but greater than placebo are shown below. The following list does not include adverse reactions 1) for which a drug cause was remote, 2) that were so general to be uninformative, or 3) that were not considered to have clinically significant implications.

- Sleep paralysis was reported in 1.6% and 1.3% of patients receiving DAYVIGO 10 mg and 5 mg, respectively, compared to no reports for placebo. Hypnagogic hallucinations were reported in 0.7% and 0.1% of patients receiving DAYVIGO 10 mg and 5 mg, respectively, compared to no reports for placebo [see Warnings and Precautions (5.2)].
- Two events of complex sleep behavior were reported, both in patients receiving DAYVIGO 10 mg [see Warnings and Precautions (5.3)].

7 DRUG INTERACTIONS

7.1 Drugs Having Clinically Important Interactions with DAYVIGO

Table 2: Clinically Important Drug Interactions with DAYVIGO
Effect of Other Drugs on DAYVIGO
Strong, Moderate, and Weak CYP3A Inhibitors
Clinical Impact: | Concomitant use with a strong, moderate, or weak CYP3A inhibitor increases lemborexant AUC and Cmax which may increase the risk of DAYVIGO adverse reactions [see Clinical Pharmacology (12.3)].
Intervention: | Avoid concomitant use of DAYVIGO with strong or moderate CYP3A inhibitors [see Dosage and Administration (2.2)]. The maximum recommended dose of DAYVIGO with weak CYP3A inhibitors is 5 mg [see Dosage and Administration (2.2)].
Examples: | Strong CYP3A inhibitors: itraconazole, clarithromycin Moderate CYP3A inhibitors: fluconazole, verapamil Weak CYP3A inhibitors: chlorzoxazone, ranitidine
Strong and Moderate CYP3A Inducers
Clinical Impact: | Concomitant use with a strong or moderate CYP3A inducer decreases lemborexant exposure, which may reduce DAYVIGO efficacy [see Clinical Pharmacology (12.3)].
Intervention: | Avoid concomitant use of DAYVIGO with strong or moderate CYP3A inducers [see Dosage and Administration (2.2)].
Examples: | Strong CYP3A inducers: rifampin, carbamazepine, St. John’s wort Moderate CYP3A inducers: bosentan, efavirenz, etravirine, modafinil
Alcohol
Clinical Impact: | Concomitant use of alcohol increases lemborexant Cmax and AUC. Co-administration of DAYVIGO with alcohol produced a numerically greater negative impact on postural stability and memory as compared with alcohol alone when assessed near the tmax of DAYVIGO (2 hours post-dose) [see Clinical Pharmacology (12.2)].
Intervention: | Avoid alcohol consumption with DAYVIGO [see Warnings and Precautions (5.1)].
Effect of DAYVIGO on Other Drugs
CYP2B6 Substrates
Clinical Impact: | Concomitant use of DAYVIGO decreases the AUC of drugs that are CYP2B6 substrates, which may result in reduced efficacy for these concomitant medications [see Clinical Pharmacology (12.3)].
Intervention: | Patients receiving DAYVIGO and CYP2B6 substrates concurrently should be monitored for adequate clinical response. Increasing the doses of CYP2B6 substrates may be considered as needed.
Examples: | Bupropion, methadone

8 USE IN SPECIFIC POPULATIONS

8.1 Pregnancy

Pregnancy Exposure Registry

There is a pregnancy exposure registry that monitors pregnancy outcomes in women who are exposed to psychiatric medications, including DAYVIGO, during pregnancy. Healthcare providers are encouraged to advise patients to register by calling the National Pregnancy Registry for Psychiatric Medications, at1-866-961-2388 or visiting online at https://womensmentalhealth.org/research/pregnancyregistry.

Risk Summary

There are no available data on DAYVIGO use in pregnant women to evaluate for drug-associated risks of major birth defects, miscarriage or adverse maternal or fetal outcomes.

In animal reproduction studies, oral administration of lemborexant to pregnant rats and rabbits during the period of organogenesis caused toxicities only at high multiples of the human exposure at the maximum recommended human dose (MRHD) based on AUC. The no observed adverse effect levels (NOAEL) are approximately >100 and 23 times the MRHD based on AUC in rats and rabbits, respectively. Similarly, oral administration of lemborexant to pregnant and lactating rats caused toxicities only at high multiples of the human exposure at the MRHD based on AUC. The NOAEL is 93 times the MRHD based on AUC (see Data).

The estimated background risk of major birth defects and miscarriage for the indicated population is unknown. All pregnancies have a background risk of birth defect, loss, or other adverse outcomes. In the U.S. general population, the estimated background risks of major birth defects and miscarriage in clinically recognized pregnancies are 2% to 4% and 15% to 20%, respectively.

Data

Animal Data

Lemborexant was administered orally to pregnant rats during the period of organogenesis in 2 studies at doses of 60, 200, and 600 mg/kg/day or 20, 60, and 200 mg/kg/day, which are approximately 6 to >300 times the MRHD based on AUC. Lemborexant caused maternal toxicity, manifested by decreased body weight and food consumption, decreased mean fetal body weight, an increased number of dead fetuses, and skeletal, external and visceral malformations (omphalocele, cleft palate, and membranous ventricular septal defect) at >300 times the MRHD based on AUC. The NOAEL of 200 mg/kg/day is approximately 143 times the MRHD based on AUC.

Lemborexant was administered orally to pregnant rabbits during the period of organogenesis at doses of 10, 30, and 100 mg/kg/day, which are approximately 7 to 139 times the MRHD based on AUC. Lemborexant caused maternal toxicity that consisted of decreased body weight and food consumption and a higher incidence of skeletal variations (presence of cervical ribs and supernumerary lung lobes) at approximately 139 times the MRHD based on AUC. The NOAEL of 30 mg/kg/day is approximately 23 times the MRHD based on AUC.

Lemborexant was administered orally to pregnant rats during pregnancy and lactation at doses of 30, 100, and 300 mg/kg/day, which are approximately 15 to 206 times the MRHD based on AUC. Lemborexant caused maternal toxicity that consisted of decreased body weight and food consumption and toxicity to offspring consisting of decreased pup body weights, decreased femur length, and decreased acoustic startle responses at 206 times the MRHD based on AUC. The NOAEL of 100 mg/kg/day is approximately 93 times the MRHD based on AUC.

8.2 Lactation

Risk Summary

Available data from a lactation study in 8 women indicates that lemborexant is transferred into the breastmilk of nursing mothers, and the results have established a mean daily infant dose of 0.0029 mg/kg/day and a relative infant dose of less than 2% of the maternal dose. These data support that transfer of lemborexant into breastmilk is low (see Data). There are no data on the effects of lemborexant on the breastfed infant, or the effects on milk production. Infants exposed to DAYVIGO through breastmilk should be monitored for excessive sedation. The developmental and health benefits of breastfeeding should be considered along with the mother’s clinical need for DAYVIGO and any potential adverse effects on the breastfed infant from DAYVIGO or from the underlying maternal condition.

Data

A single dose milk-only lactation study was conducted in 8 healthy adult lactating women. The mean amount of lemborexant recovered in human milk was 0.0174 mg following a 10 mg maternal dose. The mean calculated daily infant oral dosage was 0.0029 mg/kg/day based on nominal infant body weight of 6 kg. Approximately 70% of the total amount of lemborexant excreted in milk was excreted by 24 hours after a single maternal dose administration. There are no data on the effects of lemborexant on the breastfed infant, the effects on milk production, or infant exposure after repeated maternal dosing of lemborexant.

8.4 Pediatric Use

The safety and effectiveness of DAYVIGO have not been established in pediatric patients.

8.5 Geriatric Use

Of the total number of patients treated with DAYVIGO (n=1418) in controlled Phase 3 studies, 491 patients were 65 years and over, and 87 patients were 75 years and over. Overall, efficacy results for patients <65 years of age were similar compared to patients ≥65 years.

In a pooled analysis of Study 1 (the first 30 days) and Study 2, the incidence of somnolence in patients ≥65 years with DAYVIGO 10 mg was higher (9.8%) compared to 7.7% in patients <65 years. The incidence of somnolence with DAYVIGO 5 mg was similar in patients ≥65 years (4.9%) and <65 years (5.1%). The incidence of somnolence in patients treated with placebo was 2% or less regardless of age [see Clinical Studies (14.2)]. Because DAYVIGO can increase somnolence and drowsiness, patients, particularly the elderly, are at a higher risk of falls [see Warnings and Precautions (5.1)]. Exercise caution when using doses higher than 5 mg in patients ≥65 years old.

8.6 Renal Impairment

No dose adjustment is required in patients with mild, moderate, or severe renal impairment.

DAYVIGO exposure (AUC) was increased in patients with severe renal impairment. Patients with severe renal impairment may experience an increased risk of somnolence [see Clinical Pharmacology (12.3)].

8.7 Hepatic Impairment

DAYVIGO has not been studied in patients with severe hepatic impairment. Use in this population is not recommended [see Dosage and Administration (2.3), Clinical Pharmacology (12.3)].

DAYVIGO exposure (AUC and Cmax) and terminal half-life were increased in patients with moderate hepatic impairment (Child-Pugh class B). Dosage adjustment is recommended in patients with moderate hepatic impairment (Child-Pugh class B) [see Dosage and Administration (2.3), Clinical Pharmacology (12.3)].

DAYVIGO exposure (AUC) was increased in patients with mild hepatic impairment (Child-Pugh class A), but the terminal half-life was not changed. Patients with mild hepatic impairment may experience an increased risk of somnolence [see Clinical Pharmacology (12.3)].

8.8 Patients with Compromised Respiratory Function

Obstructive Sleep Apnea (OSA)

The respiratory depressant effect of DAYVIGO was evaluated after 8 consecutive nights of treatment with DAYVIGO 10 mg in a randomized, placebo-controlled, two-period crossover study in 37 patients with mild OSA (apnea-hypopnea index < 15 events per hour of sleep). Following once daily dosing of 10 mg, the mean treatment difference (DAYVIGO – placebo) on Day 8 for the apnea-hypopnea index was -0.06 (95% CI: -1.95 to 1.83).

DAYVIGO was also evaluated after 8 consecutive nights of treatment with DAYVIGO 10 mg in a randomized, placebo-controlled, two-period crossover study in 33 patients with moderate to severe OSA (apnea-hypopnea index ≥ 15 events per hour of sleep). Following once daily dosing of 10 mg, the mean treatment difference (DAYVIGO – placebo) on Day 8 for the apnea-hypopnea index was -0.80 (95% CI: -4.88 to 3.29).

Due to study limitations, including the short duration of the study, clinically meaningful respiratory effects of DAYVIGO in OSA cannot be excluded, including for long-term treatment [see Warnings and Precautions (5.4)].

Chronic Obstructive Pulmonary Disease (COPD)

The respiratory depressant effect of DAYVIGO was evaluated after 8 consecutive nights of treatment with DAYVIGO 10 mg in a randomized, placebo-controlled, two-period crossover study in 30 patients with moderate to severe COPD (Forced expiratory volume in the first second (FEV1)/Forced vital capacity (FVC) ratio ≤ 70% and 30% ≤ FEV1 < 80% of predicted). Following once-daily dosing of 10 mg, the mean treatment difference (DAYVIGO – placebo) on Day 8 for the mean peripheral capillary oxygen saturation during sleep was 0.47 (95% CI: 0.07 to 0.87).

DAYVIGO has not been studied in COPD patients with a FEV1 < 30% of predicted.

Clinically meaningful respiratory effects of DAYVIGO in patients with compromised respiratory function cannot be excluded [see Warnings and Precautions (5.4)].

9 DRUG ABUSE AND DEPENDENCE

9.1 Controlled Substance

DAYVIGO contains lemborexant, a Schedule IV controlled substance.

9.2 Abuse

Abuse is the intentional, non-therapeutic use of a drug, even once, for its desirable psychological or physiological effects. In a human abuse potential study conducted in recreational sedative abusers (n=29), lemborexant 10 mg, 20 mg (two times the maximum recommended dose), and 30 mg (three times the maximum recommended dose) produced responses on positive subjective measures such as “Drug Liking,” “Overall Drug Liking,” “Take Drug Again,” and “Good Drug Effects” that were statistically similar to those produced by the sedatives zolpidem (30 mg) and suvorexant (40 mg), and statistically greater than the responses on these measures that were produced by placebo. Because individuals with a history of abuse or addiction to alcohol or other drugs may be at increased risk for abuse and addiction to DAYVIGO, follow such patients carefully.

9.3 Dependence

Physical dependence is a state that develops as a result of physiological adaptation in response to repeated drug use, manifested by withdrawal signs and symptoms after abrupt discontinuation or a significant dose reduction of a drug. In animal studies and clinical trials evaluating physical dependence, chronic administration of lemborexant did not produce withdrawal signs or symptoms upon drug discontinuation. This suggests that lemborexant does not produce physical dependence.

10 OVERDOSAGE

There is limited clinical experience with DAYVIGO overdose. In clinical pharmacology studies, healthy patients who were administered multiple doses of up to 75 mg (7.5 times the maximum recommended dose) of DAYVIGO showed dose-dependent increases in the frequency of somnolence.

There is no available specific antidote to an overdose of DAYVIGO. In the event of overdose, standard medical practice for the management of any overdose should be used. In managing overdose, provide supportive care, including close medical supervision and monitoring and consider the possibility of multiple drug involvement. Consult a Certified Poison Control Center for the most up to date information on the management of overdosage (1-800-222-1222 or www.poison.org).

The value of dialysis in the treatment of overdosage has not been determined with lemborexant. As lemborexant is highly protein-bound, hemodialysis is not expected to contribute to elimination of lemborexant.

11 DESCRIPTION

DAYVIGO contains lemborexant, an orexin receptor antagonist. The chemical name of lemborexant is (1R,2S)-2-{[(2,4-dimethylpyrimidin-5-yl)oxy]methyl}-2-(3-fluorophenyl)-N-(5-fluoropyridin-2-yl) cyclopropanecarboxamide. The molecular formula is C22H20F2N4O2. The molecular weight is 410.42.

The structural formula is:

Lemborexant is a white to off-white powder that is practically insoluble in water.

DAYVIGO tablets are intended for oral administration. Each film coated tablet contains 5 mg or 10 mg of lemborexant. The inactive ingredients are: hydroxypropyl cellulose, lactose monohydrate, low-substituted hydroxypropyl cellulose, and magnesium stearate.

In addition, the film coating contains the following inactive ingredients: hypromellose 2910, polyethylene glycol 8000, talc, titanium dioxide, and either (a) ferric oxide yellow for the 5 mg tablet; or, (b) both ferric oxide yellow and ferric oxide red for the 10 mg tablet.

12 CLINICAL PHARMACOLOGY

12.1 Mechanism of Action

The mechanism of action of lemborexant in the treatment of insomnia is presumed to be through antagonism of orexin receptors. The orexin neuropeptide signaling system plays a role in wakefulness. Blocking the binding of wake-promoting neuropeptides orexin A and orexin B to receptors OX1R and OX2R is thought to suppress wake drive.

12.2 Pharmacodynamics

Lemborexant binds to orexin receptors OX1R and OX2R and acts as a competitive antagonist (IC50 values of 6.1 nM and 2.6 nM, respectively). A major metabolite of lemborexant, M10, binds with comparable affinity as the parent drug to orexin receptors OX1R and OX2R (IC50 values of 4.2 nM and 2.9 nM), respectively.

Cardiac Electrophysiology

In a concentration-QTcF analysis using the data from two randomized, double-blind, placebo-controlled, multiple ascending dose studies in healthy subjects, lemborexant does not prolong the QTcF interval to any clinically relevant extent at a dose 5 times the maximum recommended dose.

Drug Interactions

Lemborexant co-administered with alcohol produced a numerically greater negative impact on postural stability and memory as compared with alcohol alone at approximately 2 hours post-dose [see Drug Interactions 7.1].

12.3 Pharmacokinetics

Following single doses of lemborexant 2.5 to 75 mg, geometric mean Cmax and AUC0-24h increased slightly less than in proportion to dose. The extent of accumulation of lemborexant at steady-state is 1.5- to 3-fold across this dose range.

Absorption

The time to peak concentration (tmax) of lemborexant is approximately 1 to 3 hours.

Effect of Food

Lemborexant Cmax decreased by 23%, AUC0-inf increased by 18%, and tmax was delayed by 2 hours following administration of a high-fat and high-calorie meal (containing approximately 150, 250, and 500 to 600 calories from protein, carbohydrate, and fat, respectively).

Distribution

The volume of distribution of lemborexant is 1970 L. Plasma protein binding of lemborexant is approximately 88% in vitro and 94% in clinical samples. The blood to plasma concentration ratio of lemborexant is 0.65.

Elimination

Metabolism

Lemborexant is primarily metabolized by CYP3A4, and to a lesser extent by CYP3A5. The major circulating metabolite is M10.

Excretion

Following administration of an oral dose, 57.4% of the dose was recovered in the feces and 29.1% in the urine (<1% as unchanged). The effective half-life for lemborexant 5 mg and 10 mg is 17 and 19 hours, respectively.

Specific Populations

No clinically significant differences in the pharmacokinetics of lemborexant were observed based on age, sex, race/ethnicity, or body mass index. No studies have been conducted to investigate the pharmacokinetics of lemborexant in pediatric patients. Exposures of lemborexant in patients with hepatic and renal impairment are summarized in Figure 1.

Figure 1. Effects of Hepatic and Renal Impairment on Lemborexant Pharmacokinetics

Drug Interaction Studies

The effects of other drugs on the exposures of lemborexant are summarized in Figure 2. The effects of lemborexant on the exposures of other drugs are summarized in Figure 3. Based on these results, drug interactions between lemborexant and strong CYP3A inducers, strong CYP3A inhibitors, moderate CYP3A inhibitors, and CYP2B6 substrates are clinically significant [see Dosage and Administration (2.2), Drug Interactions (7.1)].

Physiologically-based pharmacokinetic (PBPK) modeling predicted that concomitant use of weak CYP3A inhibitors increased lemborexant exposure by less than 2-fold [see Dosage and Administration (2.2), Drug Interactions (7.1)], and that lemborexant is expected to have minimal effect on the pharmacokinetics of CYP2C8, CYP2C9, or CYP2C19 substrates.

Figure 2. Effects of Co-administered Drugs on the Pharmacokinetics of Lemborexant 10 mg

Figure 3. Effects of Lemborexant 10 mg on the Pharmacokinetics of Co-Administered Drugs

In Vitro Studies

In vitro metabolism studies demonstrated that lemborexant and M10 have the potential to induce CYP3A and a weak potential to inhibit CYP3A and induce CYP2B6. Lemborexant and M10 do not inhibit other CYP isoforms (CYP1A2, CYP2A6, CYP2B6, CYP2C8, CYP2C9, CYP2C19, CYP2D6, and CYP2E1) or transporters (P-gp, BCRP, BSEP, OAT1, OAT3, OATP1B1, OATP1B3, OCT1, OCT2, MATE1, and MATE2-K). Lemborexant and M10 do not induce CYP2C8, CYP2C9, and CYP2C19 at clinically relevant concentrations.

Lemborexant is a potential poor substrate of P-gp, but M10 is a substrate of P-gp. Lemborexant and M10 are not substrates of BCRP, OATP1B1, or OATP1B3.

13 NONCLINICAL TOXICOLOGY

13.1 Carcinogenesis, Mutagenesis, Impairment of Fertility

Carcinogenesis

Lemborexant did not increase the incidence of tumors in rats treated for 2 years at oral doses of 30, 100, and 300 mg/kg/day (males) and 10, 30, and 100 mg/kg/day (females), which are >80 times the MRHD based on AUC. Lemborexant did not increase the incidence of tumors in Tg ras H2 mice treated for 26 weeks at oral doses of 50, 150, and 500 mg/kg/day.

Mutagenesis

Lemborexant was not mutagenic in the in vitro bacterial reverse mutation (Ames) assay or in the in vitro mouse lymphoma thymidine kinase assay, and was not clastogenic in the in vivo rat micronucleus assay.

Impairment of Fertility

Lemborexant was orally administered to female rats at doses of 30, 100, or 1000 mg/kg/day prior to and throughout mating and continuing to gestation Day 6. These doses are approximately 12 to >500 times the MRHD based on AUC. Irregular estrous cycles and decreased pregnancy rate were observed at 60 times the MRHD based on AUC, and decreased numbers of corpora lutea, implantations, and live embryos were observed at >500 times the MRHD based on AUC. The exposure at the NOAEL of 30 mg/kg/day is approximately 12 times the MRHD based on AUC. Lemborexant did not affect fertility when orally administered to male rats at doses of 30, 100, or 1000 mg/kg/day prior to and throughout mating; the highest dose is approximately 138 times the MRHD based on AUC.

13.2 Animal Toxicology and/or Pharmacology

Lemborexant administered to mice at oral doses of 10 or 30 mg/kg resulted in behavior characteristic of cataplexy when presented with chocolate. Chocolate is a stimulus that has been demonstrated to increase cataplexy occurrences in narcoleptic mice.

14 CLINICAL STUDIES

14.1 Controlled Clinical Studies

DAYVIGO was evaluated in two clinical trials in patients with insomnia characterized by difficulties with sleep onset and/or sleep maintenance (Study 1, NCT02952820 and Study 2, NCT02783729).

Study 1 was a 6-month, randomized, double-blind, placebo-controlled, multi-center trial in adult patients age 18 or older who met DSM-5 criteria for insomnia disorder. Patients were randomized to placebo (n=325), DAYVIGO 5 mg (n=323), or DAYVIGO 10 mg (n=323) once nightly. The primary efficacy endpoint was the mean change from baseline to end of treatment at 6 months for log-transformed patient-reported (subjective) sleep onset latency (sSOL), defined as the estimated minutes from the time that the patient attempted to sleep until sleep onset. Pre-specified secondary efficacy endpoints for sleep maintenance were change from baseline to end of treatment at 6 months for patient-reported sleep efficiency (sSEF) and wake after sleep onset (sWASO). sSEF is defined as the proportion of time spent asleep per time in bed. sWASO is defined as the minutes of wake from the onset of sleep until wake time. The primary and pre-specified secondary efficacy endpoints were measured by sleep diary.

The demographic characteristics of patients in Study 1 were similar across the treatment arms. Patients had a median age of 55 years (range 18 to 88) and were 68% female, 72% White, 8% Black or African American, 17% Japanese, and 3.5% other; 28% were elderly (≥65 years).

Examination of subgroups by age, race, and sex did not suggest differences in response to DAYVIGO. In Study 1, DAYVIGO 5 mg and 10 mg demonstrated statistically significant superiority on the primary efficacy measure, sSOL, compared to placebo (Table 3). DAYVIGO 5 mg and 10 mg also showed statistically significant superiority in sSEF and sWASO.

Table 3: Primary and Secondary Efficacy Results for Change from Baseline in Sleep Onset and Sleep Maintenance at 6 Months in Patients with Insomnia (Study 1)

Endpoint | Treatment Group | Number of Patients ITT | Baseline Meana (SD) | Month 6 LS Meana (SE) | Treatment Effect (95% CI)
Sleep Onset sSOL (minutes) | DAYVIGO 5 mg* | 316 | 43.0 (31.5) | 20.0 (1.1) | 0.7 (0.6, 0.8)
 | DAYVIGO 10 mg* | 315 | 45.0 (33.4) | 19.2 (1.1) | 0.7 (0.6, 0.8)
 | Placebo | 318 | 45.0 (31.8) | 27.3 (1.4) | (ratio vs placebo)b
Sleep Maintenance sSEF (%) | DAYVIGO 5 mg* | 316 | 63.1 (18.2) | 75.9 (0.9) | 4.5 (2.2, 6.9)
 | DAYVIGO 10 mg* | 315 | 62.0 (17.2) | 75.9 (0.9) | 4.7 (2.4, 7.0)
 | Placebo | 318 | 61.3 (17.8) | 71.4 (0.8) | (%)c
Sleep Maintenance sWASO (minutes) | DAYVIGO 5 mg* | 316 | 132.8 (82.5) | 87.9 (3.7) | -17.5 (-27.3, -7.6)
 | DAYVIGO 10 mg* | 315 | 136.8 (87.4) | 92.7 (3.7) | -12.7 (-22.4, -3.0)
 | Placebo | 318 | 132.5 (80.2) | 105.3 (3.6) | (minutes)c
ITT (intention to treat); sSOL (subjective sleep onset latency); SD (standard deviation); LS (least squares); SE (standard error); CI (unadjusted confidence interval); sSEF (subjective sleep efficiency); sWASO (subjective wake after sleep onset)
a For the sleep onset sSOL endpoint, the mean refers to geometric mean, which was used due to the approximately log normal distribution of the outcomes; SD for the geometric mean is calculated as GM*SD (log transformed sSOL); SE for the least squares geometric mean is calculated in the same way as the SD.
b For the sleep onset sSOL endpoint, treatment effect refers to the ratio of [Month 6 sSOL / Baseline sSOL] for DAYVIGO versus placebo, such that a smaller ratio corresponds to a greater improvement.
c Treatment effect refers to the treatment difference between DAYVIGO versus placebo, such that a larger value for sSEF and smaller value for sWASO correspond to greater improvement.
* Doses that were statistically significantly superior (p<0.05) to placebo after multiplicity adjustment.

Study 2 was a 1-month, randomized, double-blind, placebo- and active-controlled, multi-center, parallel-group clinical trial in adult female patients age 55 and older and male patients 65 years and older who met DSM-5 criteria for insomnia disorder. Patients were randomized to placebo (n=208), DAYVIGO 5 mg (n=266) or 10 mg (n=269), or active comparator (n=263) once nightly.

The primary efficacy endpoint was the mean change in log-transformed latency to persistent sleep (LPS) from baseline to end of treatment (Days 29/30), as measured by overnight polysomnography (PSG) monitoring. LPS was defined as the number of minutes from lights off to the first 10 consecutive minutes of non-wakefulness. The pre-specified secondary efficacy endpoints in Study 2 were the mean change from baseline to end of treatment (Days 29/30) in sleep efficiency (SEF) and wake after sleep onset (WASO) measured by PSG.

The demographic and baseline characteristics of patients in Study 2 were similar across the treatment arms. Patients had a median age of 63 years (range 55 to 88) and were 86% female, 72% White, 25% Black or African American, and 2% other; 45% were elderly (≥65 years).

In Study 2, DAYVIGO 5 mg and 10 mg demonstrated statistically significant superiority on the primary efficacy measure, LPS, compared to placebo (Table 4). DAYVIGO 5 mg and 10 mg demonstrated statistically significant improvement in SEF and WASO compared to placebo.

Table 4: Primary and Secondary Efficacy Results for Change from Baseline in Sleep Onset and Sleep Maintenance at 1 Month in Patients with Insomnia (Study 2)

Endpoint | Treatment Group | Number of Patients ITT | Baseline Meana (SD) | Day 29/30 LS Meana (SE) | Treatment Effect (95% CI)
Sleep Onset LPS (minutes) | DAYVIGO 5 mg* | 266 | 33.0 (27.2) | 15.5 (0.8) | 0.8 (0.7, 0.9)
 | DAYVIGO 10 mg* | 269 | 33.3 (27.2) | 14.5 (0.7) | 0.7 (0.6, 0.8)
 | Placebo | 208 | 33.6 (25.9) | 20.0 (1.1) | (ratio vs. placebo)b
Sleep Maintenance SEF (%) | DAYVIGO 5 mg* | 266 | 68.4 (11.3) | 80.7 (0.5) | 7.1 (5.6, 8.5)
 | DAYVIGO 10 mg* | 269 | 67.8 (10.8) | 82.7 (0.5) | 8.0 (6.6, 9.5)
 | Placebo | 208 | 68.9 (9.6) | 74.6 (0.6) | (%)c
Sleep Maintenance WASO (minutes) | DAYVIGO 5 mg* | 266 | 113.4 (39.0) | 68.3 (2.2) | -24.0 (-30.0, -18.0)
 | DAYVIGO 10 mg* | 269 | 114.8 (40.0) | 66.9 (2.2) | -25.3 (-31.4, -19.3)
 | Placebo | 208 | 111.7 (37.2) | 92.2 (2.5) | (minutes)c
ITT (intention to treat); LPS (latency to persistent sleep); SD (standard deviation); LS (least squares); SE (standard error); CI (unadjusted confidence interval); SEF (sleep efficiency); WASO (wake after sleep onset)
a For the sleep onset LPS endpoint, the mean refers to geometric mean, which was used due to the approximately log normal distribution of the outcomes; SD for the geometric mean is calculated as GM*SD (log transformed LPS); SE for the least squares geometric mean is calculated in the same way as the SD.
b For the LPS endpoint, treatment effect refers to the ratio of [Day 29/30 LPS / Baseline LPS] for DAYVIGO versus placebo, such that a smaller ratio corresponds to a greater improvement.
c Treatment effect refers to the treatment difference between DAYVIGO versus placebo, such that a larger value for SEF and smaller value for WASO correspond to greater improvement.
* Doses that were statistically significantly superior (p<0.05) to placebo after multiplicity adjustment.

The effects of DAYVIGO at the beginning of treatment were generally consistent with later timepoints.

14.2 Special Safety Studies

Middle of the Night Safety

The effect of DAYVIGO on middle of the night safety was evaluated in a randomized, placebo- and active-controlled trial in healthy female subjects ≥55 years or male subjects ≥65 years. Postural stability, the ability to awaken in response to a sound stimulus, and attention and memory were assessed following a scheduled awakening 4 hours after the start of the 8-hour time in bed. Postural stability was measured by assessing body sway using an ataxia meter. Nighttime dosing of DAYVIGO 5 mg and 10 mg resulted in impairment of balance (measured by body sway area) at 4 hours as compared to placebo.

The ability to awaken to sound in the middle of the night was assessed using an audiometer that delivered 1000 Hz tones up to 105 dB. There were no meaningful differences between DAYVIGO (5 mg or 10 mg) and placebo on ability to awaken to sound.

A computerized performance assessment battery was administered to assess attention and memory after middle of the night awakening (4 hours postdose) in subjects receiving DAYVIGO 5 mg or 10 mg. DAYVIGO was associated with dose-dependent worsening on measures of attention and memory as compared to placebo.

Patients should be cautioned about the potential for middle of the night postural instability, as well as attention and memory impairment.

Effects on Next-day Postural Stability and Memory

The effects of DAYVIGO on next day postural stability and memory were evaluated in two randomized, placebo- and active-controlled trials in healthy subjects and insomnia patients age 55 and older.

There were no meaningful differences between DAYVIGO (5 mg or 10 mg) and placebo on next-day postural stability or memory compared to placebo.

Effects on Driving

A randomized, double-blind, placebo- and active-controlled, four-period crossover study evaluated the effects of nighttime administration of DAYVIGO on next-morning driving performance approximately 9 hours after dosing in 24 healthy elderly subjects (≥65 years, median age 67 years; 14 men, 10 women) and 24 adult subjects (median age 49 years; 12 men, 12 women). The primary driving performance outcome measure was change in Standard Deviation of Lateral Position (SDLP). Testing was conducted after one night (a single dose) and after eight consecutive nights of treatment with DAYVIGO. Although DAYVIGO at doses of 5 mg and 10 mg did not cause statistically significant impairment in next-morning driving performance in adult or elderly subjects (compared with placebo), driving ability was impaired in some subjects taking 10 mg DAYVIGO.

Patients using the 10 mg dose should be cautioned about the potential for next-morning driving impairment because there is individual variation in sensitivity to DAYVIGO.

Rebound Insomnia

Rebound insomnia was assessed by comparing sleep diary-recorded sSOL and sWASO from the screening period to the two weeks following treatment discontinuation in both Studies 1 and 2. Analyses of group means and the proportion of patients with rebound insomnia suggest that DAYVIGO was not associated with rebound insomnia following treatment discontinuation.

Withdrawal Effects

In 12-month and 1-month controlled safety and efficacy trials (Studies 1 and 2, respectively), withdrawal effects were assessed by the Tyrer Benzodiazepine Withdrawal Symptom Questionnaire following discontinuation from study drug in patients who received DAYVIGO 5 mg or 10 mg. There was no evidence of withdrawal effects following DAYVIGO discontinuation at either dose.

16 HOW SUPPLIED/STORAGE AND HANDLING

16.1 How Supplied

DAYVIGO tablets are available as:

- 5 mg, pale yellow, round, biconvex, film-coated tablets, and debossed with "5" on one side and "LЄM" on the other side.

NDC 62856-405-30, bottle of 30 with child-resistant closure

NDC 62856-405-90, bottle of 90 with child-resistant closure

- 10 mg, orange, round, biconvex, film-coated tablets, and debossed with "10" on one side and "LЄM" on the other side.

NDC 62856-410-30, bottle of 30 with child-resistant closure

NDC 62856-410-90, bottle of 90 with child-resistant closure

16.2 Storage and Handling

Store at 20°C to 25°C (68°F to 77°F), excursions permitted between 15°C and 30°C (59°F and 86°F) [See USP Controlled Room Temperature].

17 PATIENT COUNSELING INFORMATION

Advise the patient to read the FDA-approved patient labeling (Medication Guide).

Administration Instructions

Advise patients to take DAYVIGO only when preparing for or getting into bed and only if they can stay in bed for a full night (at least 7 hours) before being active again [see Dosage and Administration (2.1)].

Advise patients that the effect of DAYVIGO may be delayed if taken with or soon after a meal [see Dosage and Administration (2.1), Clinical Pharmacology (12.3)].

CNS Depressant Effects and Daytime Impairment

Advise patients that DAYVIGO can impair daytime wakefulness even when used as prescribed. The risk of daytime impairment is increased if DAYVIGO is taken with less than a full night of sleep remaining or if a higher than recommended dose is taken. If DAYVIGO is taken in these circumstances, caution patients against driving and other activities requiring complete mental alertness. Advise patients that increased drowsiness may increase the risk of falls in some patients [see Warnings and Precautions (5.1)].

Sleep Paralysis, Hypnagogic/Hypnopompic Hallucinations, and Cataplexy-Like Symptoms

Advise patients and their families that DAYVIGO may cause sleep paralysis, which is an inability to move or speak for several minutes during sleep-wake transitions, despite being aware of surroundings; hypnagogic/hypnopompic hallucinations, including vivid and disturbing perceptions; and symptoms similar to mild cataplexy [see Warnings and Precautions (5.2)].

Complex Sleep Behaviors

Instruct patients and their families that DAYVIGO may cause complex sleep behaviors, including sleep-walking, sleep-driving, preparing and eating food, making phone calls, or having sex while not being fully awake. Tell patients to discontinue DAYVIGO and notify their healthcare provider immediately if they develop any of these symptoms [see Warnings and Precautions (5.3)].

Worsening of Depression/Suicidal Ideation

Tell patients to report any worsening of depression or suicidal thoughts immediately [see Warnings and Precautions (5.4)].

Pregnancy

Advise patients that there is a pregnancy exposure registry that monitors pregnancy outcomes in women exposed to DAYVIGO during pregnancy [see Use in Specific Populations (8.1)].

Concomitant Medications

Ask patients about alcohol consumption, medicines they are taking, and drugs they may be taking without a prescription. Advise patients not to consume alcohol in combination with DAYVIGO [see Drug Interactions (7.1), Clinical Pharmacology (12.3)].

Tolerance, Abuse, and Dependence

Tell patients not to increase the dose of DAYVIGO on their own, and to inform you if they believe the drug “does not work” [see Drug Abuse and Dependence (9)].

Distributed by:
Eisai Inc.
Nutley, NJ 07110

DAYVIGO® is a registered trademark of Eisai R&D Management Co., Ltd. and is licensed to Eisai Inc.

© 2019-2025 Eisai Inc.

MEDICATION GUIDE
DAYVIGO® (daye-vi'-goe)
(lemborexant)
tablets, for oral use, CIV

What is the most important information I should know about DAYVIGO?
DAYVIGO may cause serious side effects including:

- Decreased awareness and alertness. The morning after you take DAYVIGO, your ability to drive safely and think clearly may be decreased. You may also have sleepiness during the day.
  ○ Do not take more DAYVIGO than prescribed.
  ○ Do not take DAYVIGO unless you are able to stay in bed for a full night (at least 7 hours) before you must be active again.
  ○ Take DAYVIGO right before going to bed.

See “What are the possible side effects of DAYVIGO?” for more information about side effects.

What is DAYVIGO?

- DAYVIGO is a prescription medicine for adults who have trouble falling or staying asleep (insomnia).
- It is not known if DAYVIGO is safe and effective in children under the age of 18 years.

DAYVIGO is a federally controlled substance (CIV) because it can be abused or cause dependence. Keep DAYVIGO in a safe place to prevent misuse and abuse. Selling or giving away DAYVIGO may harm others and is against the law. Tell your doctor if you have ever abused or have been dependent on alcohol, prescription medicines or street drugs.

Who should not take DAYVIGO?
Do not take DAYVIGO if you fall asleep often at unexpected times (narcolepsy).

Before taking DAYVIGO, tell your healthcare provider about all of your medical conditions, including if you:

- have a history of depression, mental illness, or suicidal thoughts.
- have a history of drug or alcohol abuse or addiction.
- have a history of a sudden onset of muscle weakness (cataplexy).
- have a history of daytime sleepiness.
- have lung problems or breathing problems.
- have liver problems.
- are pregnant or plan to become pregnant. It is not known if DAYVIGO can harm your unborn baby.

- Pregnancy Registry: There is a pregnancy registry for women who are exposed to DAYVIGO during pregnancy or who become pregnant while taking DAYVIGO. The purpose of this registry is to collect information about the health of you and your baby. For more information or to participate in the registry, call 1-866-961-2388 or go to https://womensmentalhealth.org/research/pregnancyregistry. Talk with your healthcare provider about the risk to your unborn baby if you take DAYVIGO during pregnancy.

- are breastfeeding or plan to breastfeed. DAYVIGO passes into your breastmilk. Talk to your healthcare provider about the best way to feed your baby during treatment with DAYVIGO.

Tell your healthcare provider about all of the medicines you take, including prescription and over-the-counter medicines, vitamins and herbal supplements.

- Taking DAYVIGO with certain other medicines can cause serious side effects. DAYVIGO may affect the way other medicines work and other medicines may affect the way DAYVIGO works.
- Do not take DAYVIGO with other medicines that can make you sleepy unless your healthcare provider tells you to.
- Know the medicines you take. Keep a list of your medicines with you to show your healthcare provider and pharmacist each time you get a new medicine.

How should I take DAYVIGO?

- Take DAYVIGO exactly as your healthcare provider tells you to take it.
- Only take DAYVIGO one time each night, right before going to bed.
- Only take DAYVIGO when you can stay in bed for a full night (at least 7 hours).
- DAYVIGO may take longer to work if you take it with or soon after a meal.
- Do not increase your dose of DAYVIGO without talking to your healthcare provider first. Call your healthcare provider if your insomnia (sleep problem) worsens or is not improved within 7 to 10 days. This may mean that there is another condition causing your sleep problem.
- If you take too much DAYVIGO, call your healthcare provider or go to the nearest hospital emergency room right away.

What should I avoid while taking DAYVIGO?

- Do not drink alcohol while taking DAYVIGO. It can increase your chances of getting serious side effects.
- Do not drive, operate heavy machinery, do anything dangerous, or do other activities that require clear thinking if you take DAYVIGO and have had less than a full night of sleep (at least 7 hours) or if you have taken more DAYVIGO than prescribed by your healthcare provider.
- You may still feel drowsy the next day after taking DAYVIGO. Do not drive or do other dangerous activities until you feel fully awake.

What are the possible side effects of DAYVIGO? See “What is the most important information I should know about DAYVIGO?”
DAYVIGO may cause serious side effects, including:

- temporary inability to move or talk (sleep paralysis) for up to several minutes while you are going to sleep or waking up.
- temporary weakness in your legs that can happen during the day or at night.
- complex sleep behaviors such as sleep-walking, sleep-driving, preparing and eating food, making phone calls, having sex or doing other activities while not fully awake that you may not remember the next morning. Call your healthcare provider right away if you experience a complex sleep behavior.
- worsening depression and suicidal thoughts have happened during treatment with DAYVIGO. Call your healthcare provider right away if you have any worsening depression or thoughts of suicide or dying.

The most common side effect of DAYVIGO is sleepiness.
These are not all of the possible side effects of DAYVIGO. Call your doctor for medical advice about side effects. You may report side effects to FDA at 1-800-FDA-1088.

How should I store DAYVIGO?

- Store DAYVIGO at room temperature between 68°F to 77°F (20°C to 25°C).
- Keep DAYVIGO and all medicines out of the reach of children.

General information about the safe and effective use of DAYVIGO.
Medicines are sometimes prescribed for purposes other than those listed in a Medication Guide. Do not use DAYVIGO for a condition for which it was not prescribed. Do not give DAYVIGO to other people, even if they have the same symptoms that you have. It may harm them. You can ask your healthcare provider or pharmacist for information about DAYVIGO that is written for healthcare professionals.

What are the ingredients in DAYVIGO?
Active ingredient: lemborexant
Inactive ingredients: hydroxypropyl cellulose, lactose monohydrate, low-substituted hydroxypropyl cellulose, and magnesium stearate. The tablet film coating contains: hypromellose 2910, polyethylene glycol 8000, talc, titanium dioxide, and either ferric oxide yellow for the 5 mg tablet; or both ferric oxide yellow and ferric oxide red for the 10 mg tablet.

Distributed by:
Eisai Inc.
Nutley, NJ 07110
DAYVIGO® is a registered trademark of Eisai R&D Management Co., Ltd. and is licensed to Eisai Inc.
© 2019-2025 Eisai Inc.
For more information, go to www.DAYVIGO.com or call 1-888-274-2378

This Medication Guide has been approved by the U.S. Food and Drug Administration. Revised: 2/2025

PRINCIPAL DISPLAY PANEL

NDC 62856-405-30
DAYVIGO
(lemborexant) tablets
5 mg
30 Tablets

PRINCIPAL DISPLAY PANEL

NDC 62856-405-90
DAYVIGO
(lemborexant) tablets
5 mg
90 Tablets

PRINCIPAL DISPLAY PANEL

NDC 62856-410-30
DAYVIGO
(lemborexant) tablets
10 mg
30 Tablets

PRINCIPAL DISPLAY PANEL

NDC 62856-410-90
DAYVIGO
(lemborexant) tablets
10 mg
90 Tablets

PRINCIPAL DISPLAY PANEL

NDC 62856-405-10
DAYVIGO
(lemborexant) tablets
5 mg
Professional Sample: Not for Sale

PRINCIPAL DISPLAY PANEL

NDC 62856-455-10
DAYVIGO
(lemborexant) tablets
5 mg
Professional Sample: Not for Sale